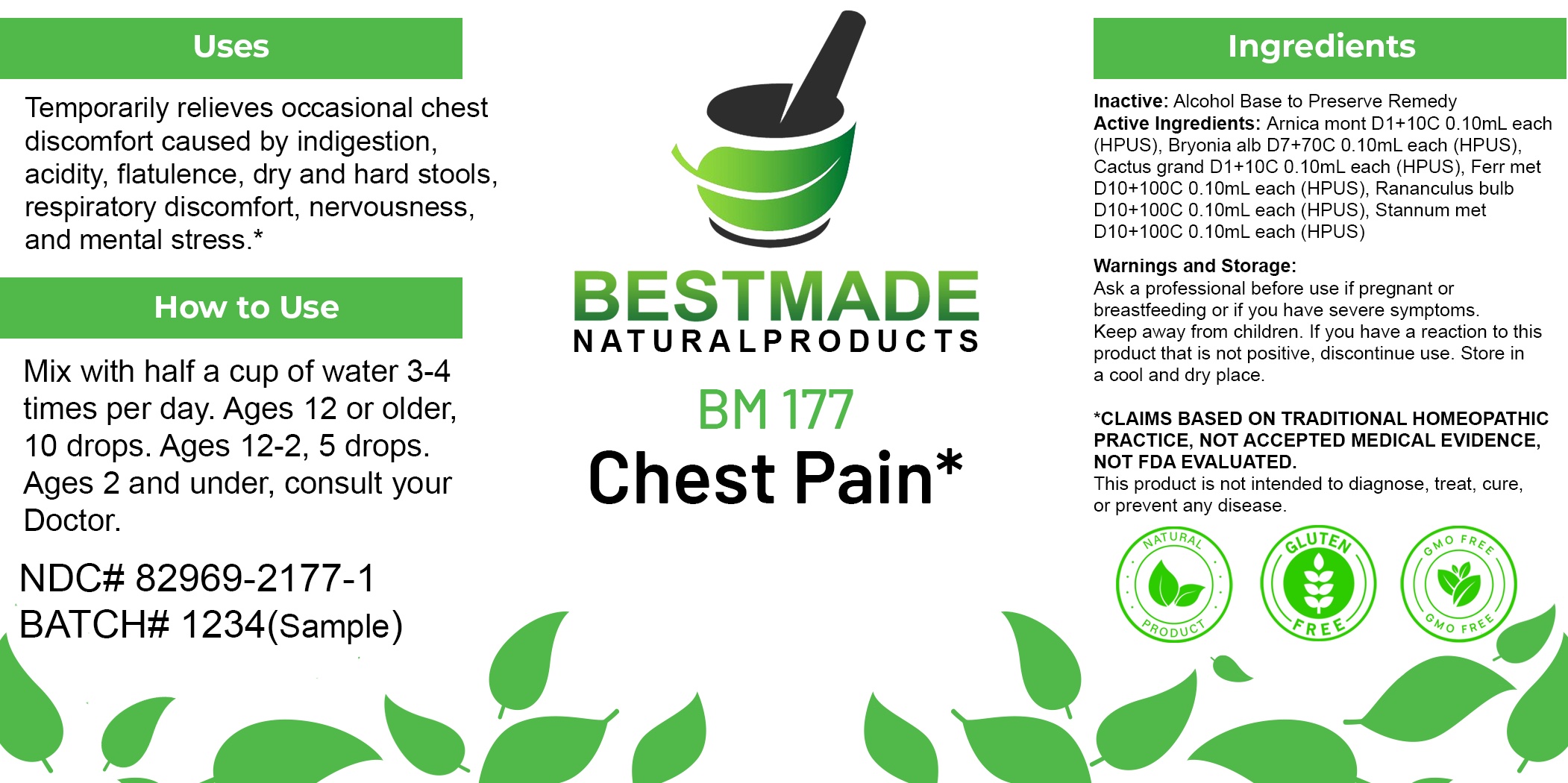 DRUG LABEL: Bestmade Natural Products BM177
NDC: 82969-2177 | Form: LIQUID
Manufacturer: Bestmade Natural Products
Category: homeopathic | Type: HUMAN OTC DRUG LABEL
Date: 20250219

ACTIVE INGREDIENTS: BRYONIA ALBA ROOT 30 [hp_C]/30 [hp_C]; IRON 30 [hp_C]/30 [hp_C]; TIN 30 [hp_C]/30 [hp_C]; ARNICA MONTANA WHOLE 30 [hp_C]/30 [hp_C]; SELENICEREUS GRANDIFLORUS STEM 30 [hp_C]/30 [hp_C]; RANUNCULUS BULBOSUS WHOLE 30 [hp_C]/30 [hp_C]
INACTIVE INGREDIENTS: ALCOHOL 30 [hp_C]/30 [hp_C]

BM177

DOSAGE AND ADMINISTRATION

How to Use

Mix with half a cup of water 3-4 times per day. Ages 12 or older, 10 drops. Ages 12-2, 5 drops. Ages 2 and under, consult your Doctor.

Inactive:

Alcohol Base to Preserve Product

ACTIVE INGREDIENTS

Arnica mont D1+10C 0.10mL each (HPUS), Bryonia alb D7+70C 0.10mL each (HPUS), Cactus grand D1+10C 0.10mL each (HPUS), Ferr met D10+100C 0.10mL each (HPUS), Rananculus bulb D10+100C 0.10mL each (HPUS), Stannum met D10+100C 0.10mL each (HPUS)

Uses

Temporarily relieves occasional chest discomfort caused by indigestion, acidity, flatulence, dry and hard stools, respiratory discomfort, nervousness, and mental stress.*

Uses
Temporarily relieves occasional chest discomfort caused by indigestion, acidity, flatulence, dry and hard stools, respiratory discomfort, nervousness, and mental stress.*

KEEP OUT OF REACH OF CHILDREN

Warnings and Storage:

Ask a professional before use if pregnant or breastfeeding or if you have severe symptoms.

Keep away from children. If you have a reaction to this product that is not positive, discontinue use. Store in a cool and dry place

*CLAIMS BASED ON TRADITIONAL HOMEOPATHIC PRACTICE, NOT ACCEPTED MEDICAL EVIDENCE NOT FDA EVALUATED.
This product is not intended to diagnose, treat, cure, or prevent any disease.

Warnings and Storage:

Ask a professional before use if pregnant or breastfeeding or if you have severe symptoms.

Keep away from children. If you have a reaction to this product that is not positive, discontinue use. Store in a cool and dry place

*CLAIMS BASED ON TRADITIONAL HOMEOPATHIC PRACTICE, NOT ACCEPTED MEDICAL EVIDENCE NOT FDA EVALUATED.
This product is not intended to diagnose, treat, cure, or prevent any disease.

Entire package label